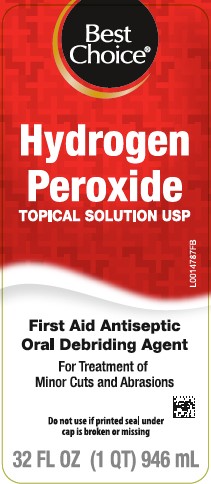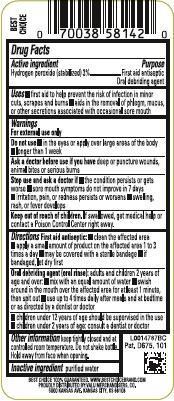 DRUG LABEL: Hydrogen Peroxide
NDC: 63941-871 | Form: SOLUTION
Manufacturer: Valu Merchandisers Company
Category: otc | Type: HUMAN OTC DRUG LABEL
Date: 20260216

ACTIVE INGREDIENTS: HYDROGEN PEROXIDE 30 mg/1 mL
INACTIVE INGREDIENTS: WATER

Best Choice 871.001/871AA
Hydrogen Peroxide

Active ingredient

Hydrogen peroxide (stabilized) 3%

Purpose

First aid antiseptic

Oral debriding agent

Uses

- first aid to help prevent the risk of infection in minor cuts, scrapes and burns
- aids in the removal of phlegm, mucus, or other secretions associated with occasional sore mouth

Warnings

For external use only

Do not use

- in the eyes or apply over large areas of the body
- longer than 1 week

Ask a doctor before use if you have

deep or puncture wounds, animal bites or serious burns

Stop Use and ask a doctor if

- the condition persists or gets worse
- sore mouth symptoms do not improve in 7 days
- irritation, pain, or redness persists or worsens
- swelling, rash, or fever develops

Keep out of reach of children.

If swallowed, get medical help or contact a Poison Control Center right away.

Directions

First Aid Antiseptic:

- clean the affected area
- apply a small amount of the product on the affected area 1 to 3 times a day
- may be covered with a sterile bandage
- if bandaged, let dry first

Oral Debriding Agent (oral rinse): adults, children over 2 years of age:

- mix with equal amount of water
- swish around in the mouth over the affected area for at least 1 minute, then spit out
- use up to 4 times daily after meals and at bedtime or as directed by a dentist or doctor

- children under 12 years of age should be supervised in the use
- children under 2 years of age: consult a dentist or doctor

Other information

Keep tightly closed and at controlled room temperature. Do not shake bottle. Hold away from face when opening.

Inactive ingredient

purified water

ADVERSE REACTION

Best Choice 100% guaranteed. WWW.BESTCHOICEBRAND.COM

PROUDLY DISTRIBUTED BY: VALU MERCHANDISERS CO.

5000 KANSAS AVE. KANSAS CITY, KS 66106

Pat. D675, 101

principal display panel

Best Choice®

Hydrogen Peroxide

TOPICAL SOLUTION USP

First Aid Antiseptic

Oral Debriding Agent

For Treatment of Minor Cuts and Abrasions

Do not use if printed seal under cap is broken or missing

32 FL OZ (1 QT) 946 mL